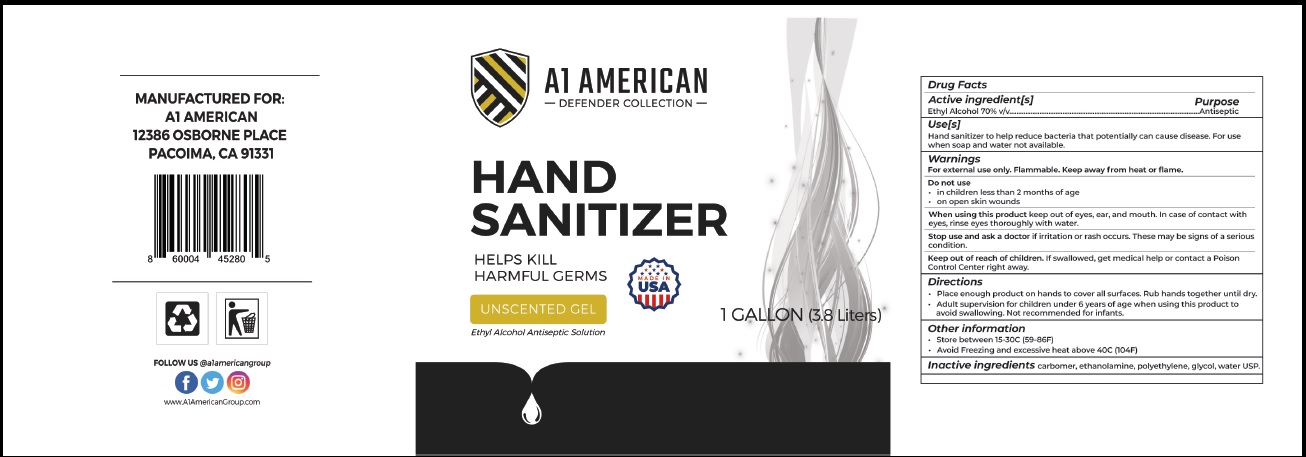 DRUG LABEL: Defender Collection
NDC: 78940-002 | Form: GEL
Manufacturer: Tiger Hospitality, LLC dba A1 American
Category: otc | Type: HUMAN OTC DRUG LABEL
Date: 20221227

ACTIVE INGREDIENTS: ALCOHOL 70 mL/100 mL
INACTIVE INGREDIENTS: PROPYLENE GLYCOL; WATER; CARBOMER 940; MONOETHANOLAMINE

Active Ingredient

Ethyl Alcohol 70% v/v.

Purpose

Antiseptic

Uses

Hand Sanitizer to help reduce bacteria that potentially can cause disease. For use when soap and water are not available.

Warnings

For external use only. Flammable. Keep away from heat or flame.

Do not use

in children less than 2 months of age
on open skin wounds

When using this product keep out of eyes, ears, and mouth. In case of contact with eyes, rinse eyes thoroughly with water.

Stop use and ask a doctor if irritation or rash occurs. These may be signs of a serious condition.

Keep out of reach of children. If swallowed, get medical help or contact a Poison Control Center right away.

Directions

- Place enough product on hands to cover all surfaces. Rub hands together until dry.
- Adult supervision for children under 6 years of age when using this product to avoide swallowing.
- Not recommended for infants.

Other information

- Store between 15-30C (59-86F)
- Avoid freezing and excessive heat above 40C (104F)

Inactive ingredients

Carbomer, ethanolamine, polyethylene glycol, water USP.